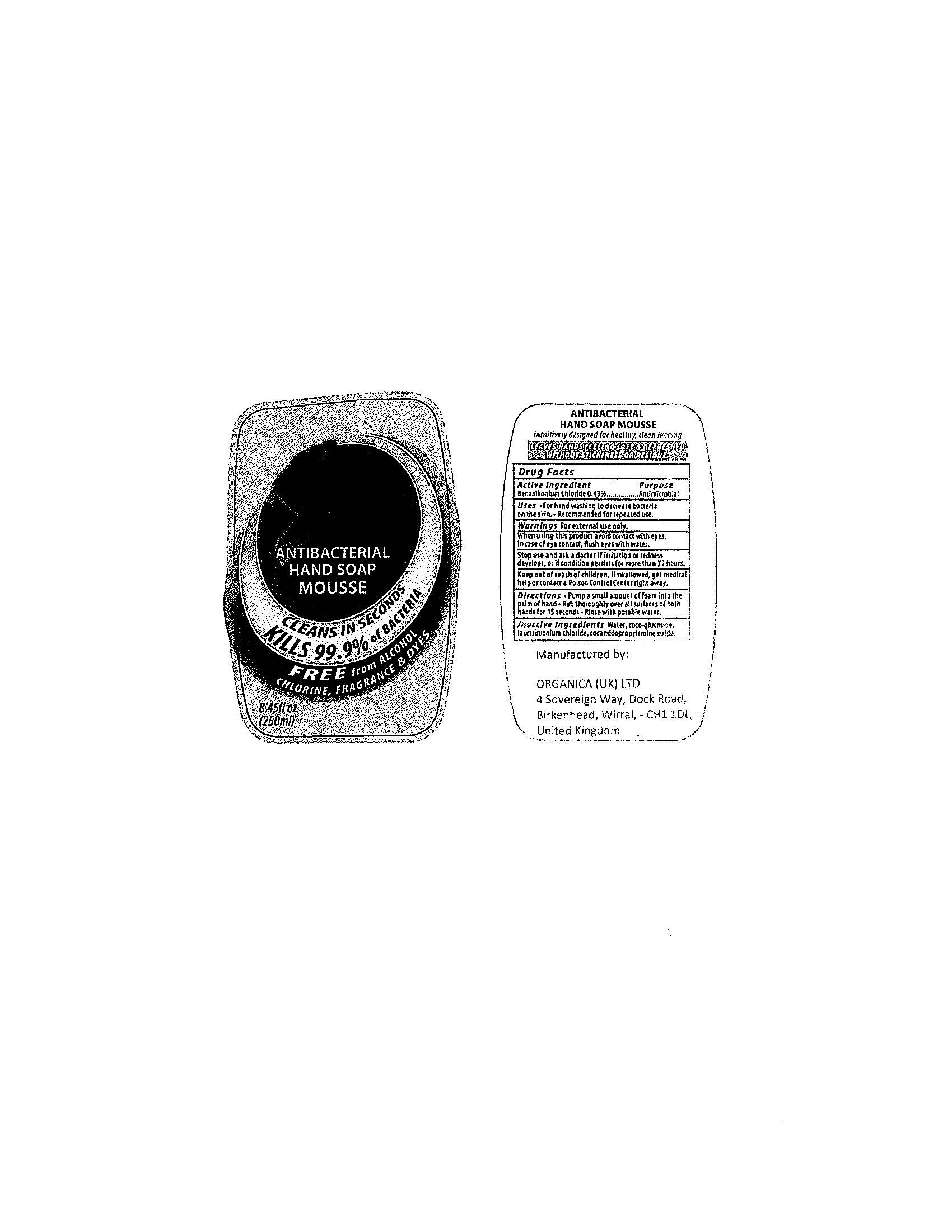 DRUG LABEL: Antibacterial Hand Mousse
NDC: 76268-002 | Form: LIQUID
Manufacturer: ORGANICA (UK) LTD
Category: otc | Type: HUMAN OTC DRUG LABEL
Date: 20111213

ACTIVE INGREDIENTS: BENZALKONIUM CHLORIDE 0.13 mL/100 mL
INACTIVE INGREDIENTS: WATER; COCO GLUCOSIDE; COCAMIDOPROPYLAMINE OXIDE; LAURTRIMONIUM CHLORIDE

Drug Facts

Active ingredient

Benzalkonium Chloride 0.13%

Purpose

Antimicrobial

Uses

For handwashing to decrease bacteria on skin.

Recommended for repeated use.

Warnings

For external use only.

When using this product avoid contact with eyes.

In case of eye contact, flush eyes with water.

Stop use and ask a doctor if irritation or redness develops, or if conditions persists for more than 72 hours.

Keep out of reach of children.

If swallowed, get medical help or contact a Poison Control Center right away.

Directions

Pump a small amount of foam into the palm of hand

Rub thoroughly over all surfaces of both hands for 15 seconds

Rinse with potable water.

Inactive ingredients

Water, coco-glucoside, laurtrimonium chloride, cocamidopropylamine oxide.

PACKAGE LABEL

ANTIBACTERIAL

HAND SOAP

MOUSSE

CLEANS IN SECONDS

KILLS 99.9% of BACTERIA

FREE from ALCOHOL

CHLORINE, FRAGRANCE and DYES

8.45fl oz

(250ml)